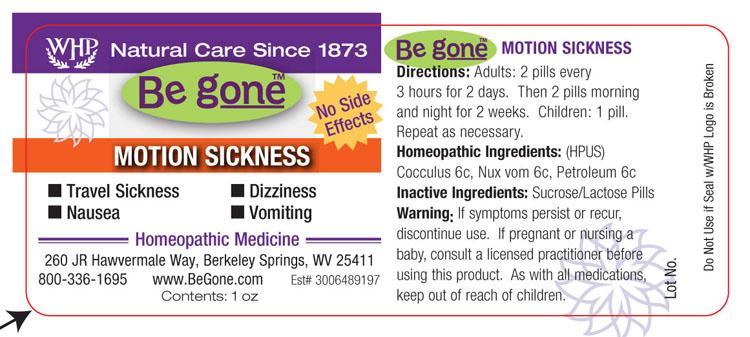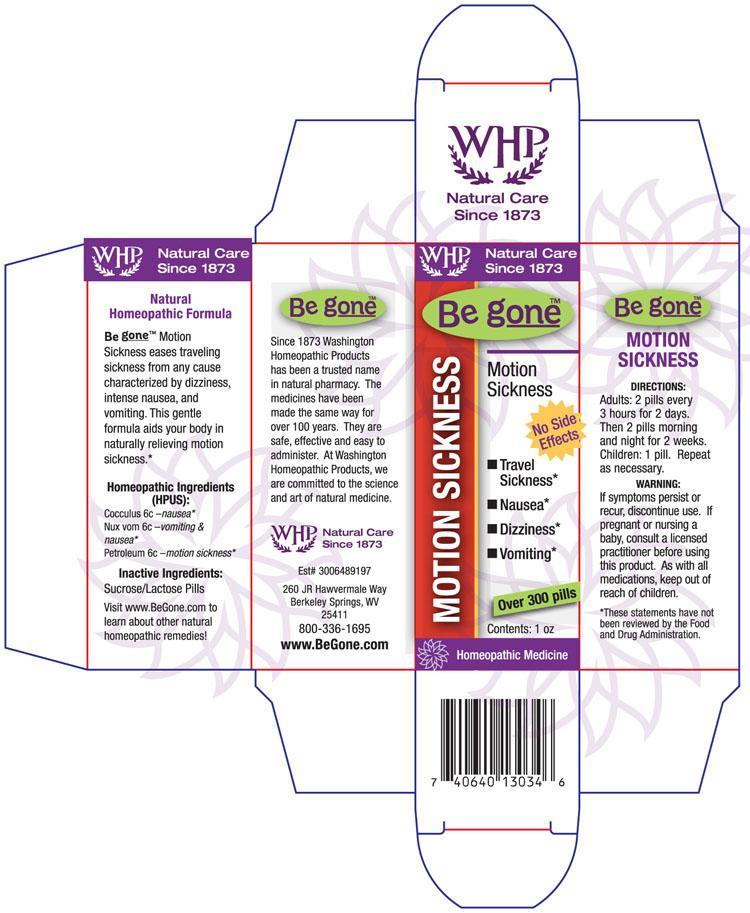 DRUG LABEL: Be gone Motion Sickness
NDC: 68428-729 | Form: PELLET
Manufacturer: Washington Homeopathic Products
Category: homeopathic | Type: HUMAN OTC DRUG LABEL
Date: 20191223

ACTIVE INGREDIENTS: ANAMIRTA COCCULUS SEED 6 [hp_C]/28 g; STRYCHNOS NUX-VOMICA SEED 6 [hp_C]/28 g; KEROSENE 6 [hp_C]/28 g
INACTIVE INGREDIENTS: SUCROSE; LACTOSE

DRUG FACTS

ACTIVE INGREDIENTS

COCCULUS 6C

NUX VOM 6C

PETROLEUM 6C

USES

To relieve the symptoms of traveling sickness from any cause characterized by dizziness, intense nausea, vomiting.

KEEP OUT OF REACH OF CHILDREN

As with all medications, keep out of reach of children.

INDICATIONS

COCCULUS Motion sickness

NUX VOM Vomiting

PETROLEUM Nausea

STOP USE AND ASK DOCTOR

If symptoms persistor recur, discontinue use. If pregnant or nursing a baby, consult a licensed practitioner before using this product.

DIRECTIONS

Adults 2 pills every 3 hours for 2 days. Then 2 pills morning and night for 2 weeks.

Children: 1 pills. Repeat as necessary.

INACTIVE INGREDIENTS

Sucrose/Lactose

PRINCIPAL DISPLAY PANEL

Be g oneTM Motion Sickness label

Be g oneTM Motion Sickness box